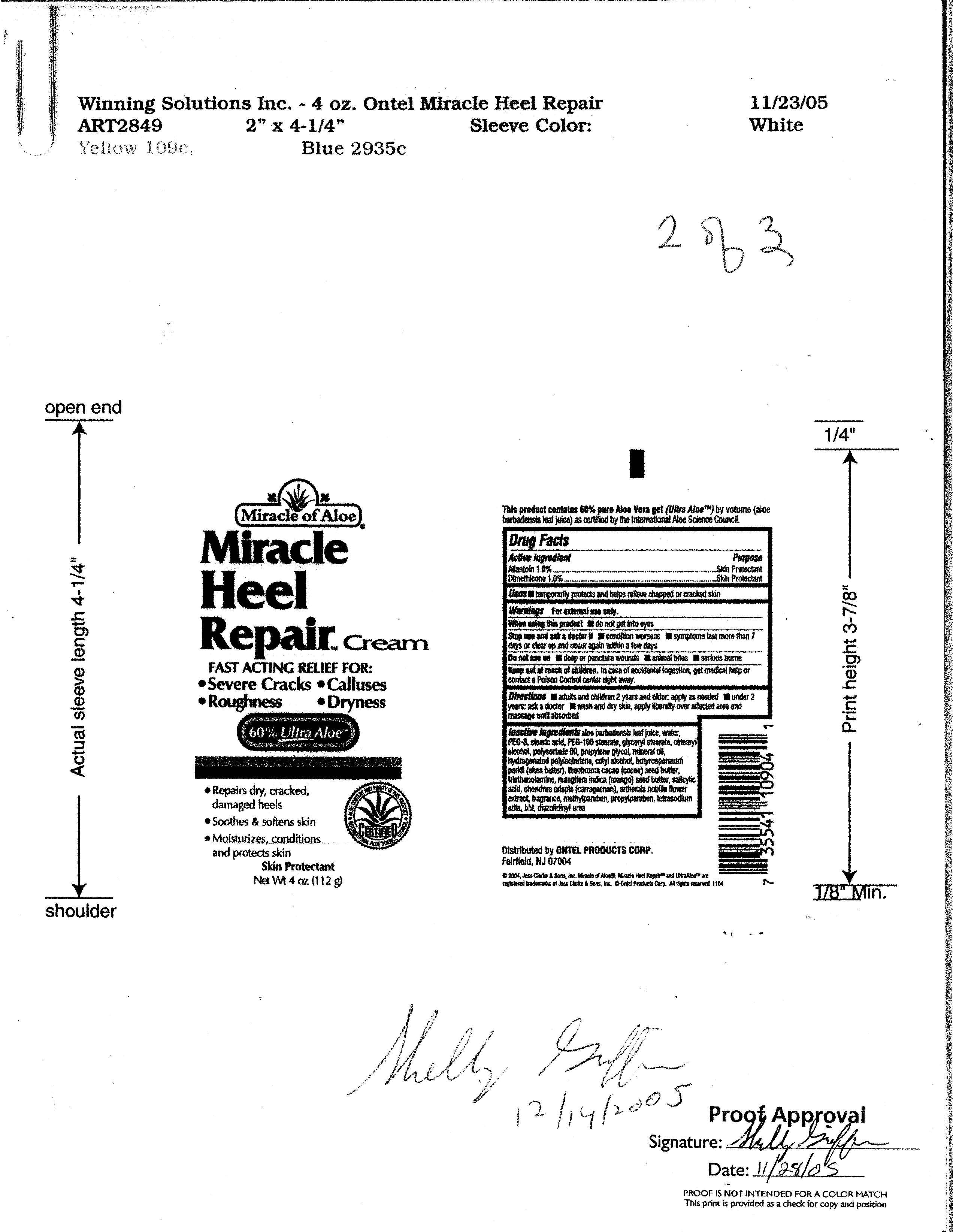 DRUG LABEL: Miracle Heel Repair  
NDC: 66391-0604 | Form: CREAM
Manufacturer: Winning Solutions
Category: otc | Type: HUMAN OTC DRUG LABEL
Date: 20110318

ACTIVE INGREDIENTS: Allantoin  1.12 g/112 g; Dimethicone  1.12 g/112 g
INACTIVE INGREDIENTS: ALOE VERA LEAF ; Water; POLYETHYLENE GLYCOL 400; Stearic Acid; PEG-100 STEARATE; GLYCERYL MONOSTEARATE; CETOSTEARYL ALCOHOL; POLYSORBATE 60; PROPYLENE GLYCOL; Mineral Oil; Cetyl Alcohol; SHEA BUTTER ; COCOA BUTTER; TROLAMINE; MANGO; SALICYLIC ACID; CHONDRUS; CHAMOMILE; Methylparaben; Propylparaben; EDETATE SODIUM; BUTYLATED HYDROXYTOLUENE

Active Ingredient : Allantoin 1.0 % , Dimethicone 1.0 %

Purpose : Skin Protectant

Warnings: For external use only .

Keep out of reach of children : In case of accidental ingestion, get medical help or contact a Poison Control center right away.

DOSAGE AND ADMINISTRATION

Directions : adults and children 2 years and older apply as needed

under 2 years ask a doctor.

wash and dry skin apply liberatly over attached area and massage until absorbed .

INDICATIONS AND USAGE

Uses: Temporary protects and helps relieve chapped or cracked skin

INACTIVE INGREDIENT

aloe barabardensis leaf Juice , water , PEG 8, stearic acid , PEG-100 stearte , glyceryl stearate , cetearyl alcohol, polysorbate 60 , propylene glycol, mineral oil ,hydrogenated polyisobutene,cetyl alcohl , butyrospermum parkii (shea butter) , theobroma cacao (cocoa) seed butter , triethanolamine, mangifera indica (mango) seed butter, salicylic acid ,chondrus crispis (carageenan) , arthemis nobilis flower extract, fragrance, methylparaben, propylparaben, tetrasodium edta , bht, diazolidinyl urea